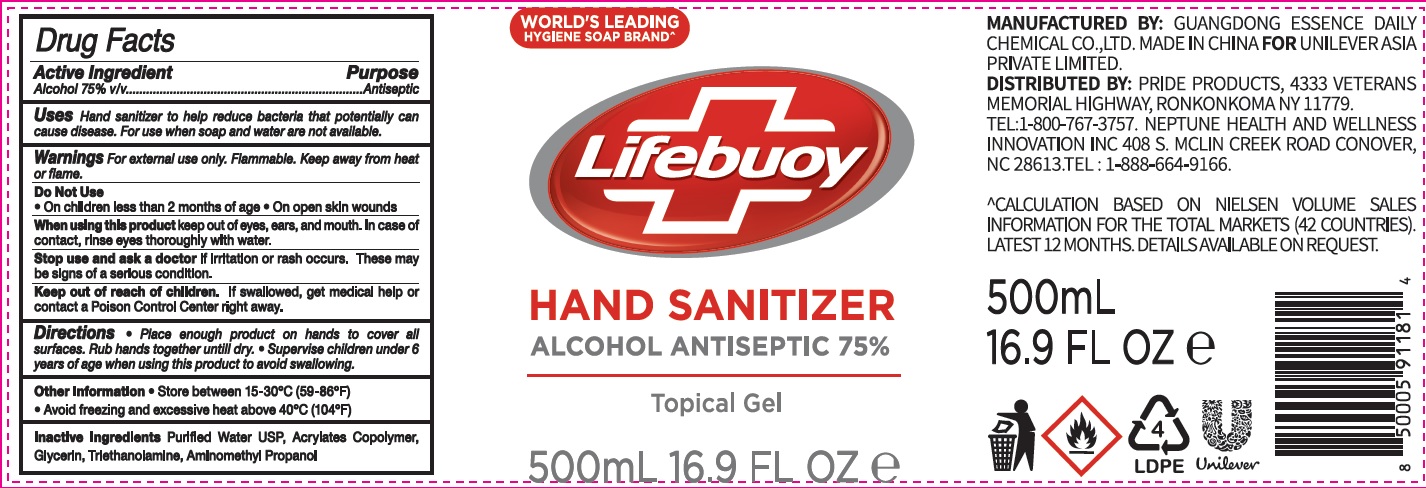 DRUG LABEL: Lifebuoy Hand Sanitizer
NDC: 73931-015 | Form: GEL
Manufacturer: Guangdong Essence Daily Chemical Co., Ltd
Category: otc | Type: HUMAN OTC DRUG LABEL
Date: 20200827

ACTIVE INGREDIENTS: ALCOHOL 75 mL/100 mL
INACTIVE INGREDIENTS: WATER; GLYCERIN; TROLAMINE; AMINOMETHYLPROPANOL

Active ingredient

Alcohol 75% v/v

purpose

antiseptic

Use

Hand sanitizer to help reduce bacteria that potentially can cause disease. For use when soap and water are not available.

Warnings

For external use only.

Flammable, Keep away from heat or flame.

Do not use

- Onchildren less than 2 months of age
- On open skin wounds

When using this product

keep out of eyes, ears, and mouth. In case of contact, rinse eyes thoroughly with water.

Stop use and ask a doctor if

irritation or rash occurs. These may be signs of a serious condition.

Keep out of reach of children.

If swallowed, get medical help or contact a Poison Control Center right away.

Directions

- Place enough product on hands to cover all surfaces. Rub hands together until dry
- Supervise children under 6 years of age when using this product to avoid swallowing.

Inactive ingredients

Purified Water USP, Acrylates Copolymer, Glycerin, Triethanolamine, Aminomethyl Propanol

other information

- Store between 15-30℃ (59-86 ℉)
- Avoid freezing and excessive heat above 40℃(104℉)